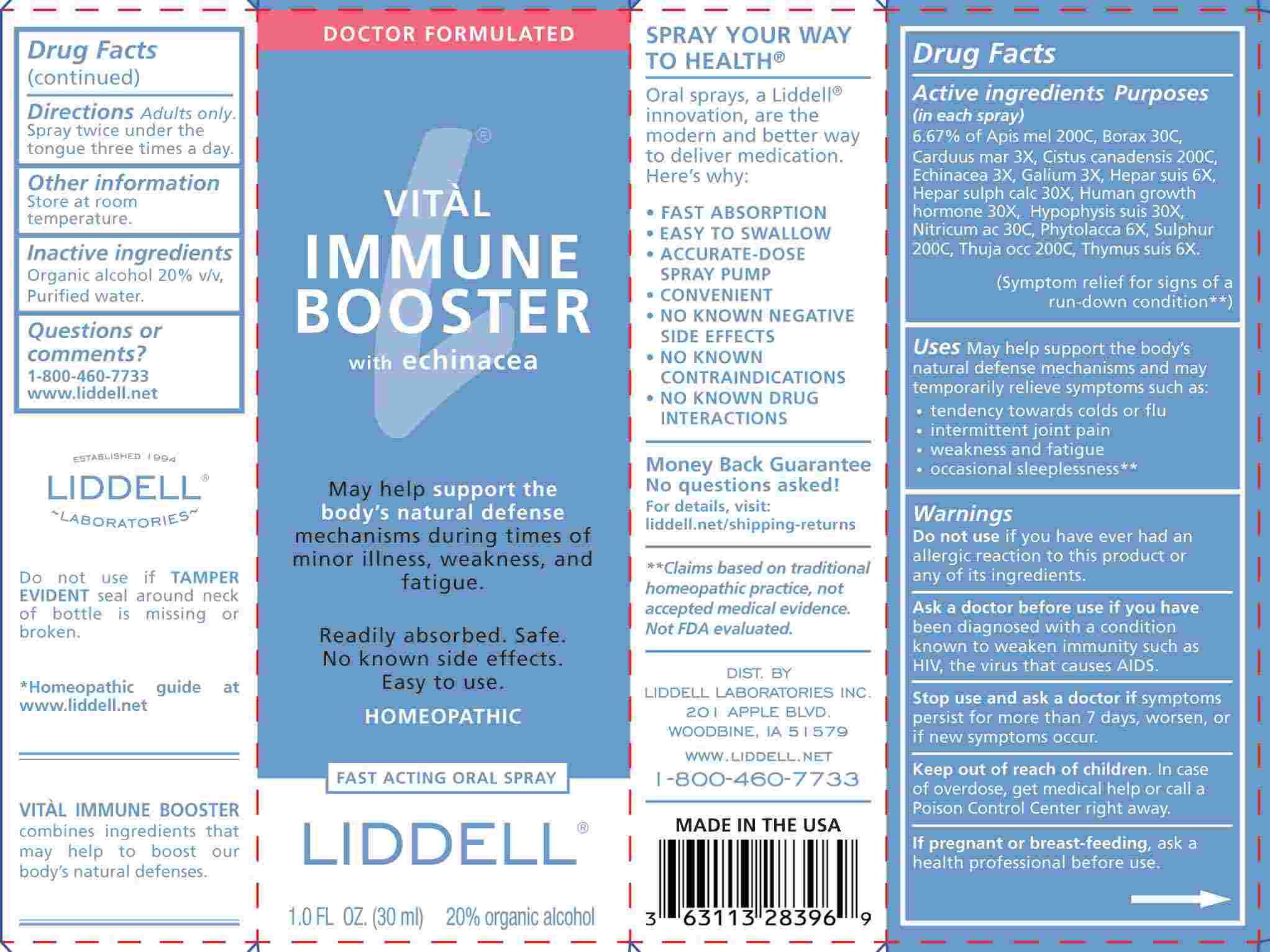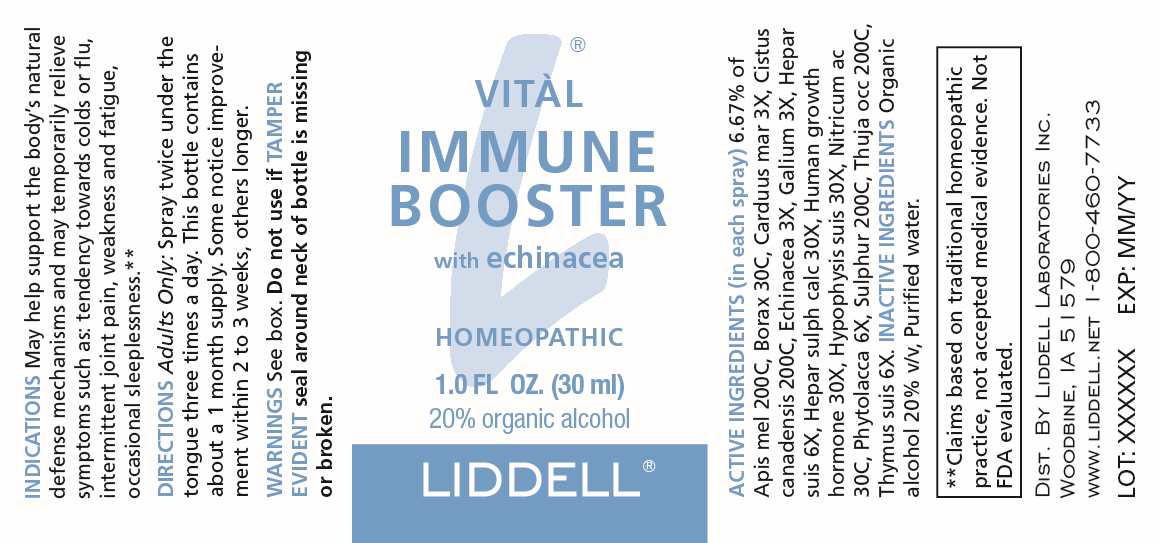 DRUG LABEL: Vital Immune Booster
NDC: 50845-0283 | Form: SPRAY
Manufacturer: Liddell Laboratories, Inc.
Category: homeopathic | Type: HUMAN OTC DRUG LABEL
Date: 20250131

ACTIVE INGREDIENTS: APIS MELLIFERA 200 [hp_C]/1 mL; SODIUM BORATE 30 [hp_C]/1 mL; MILK THISTLE 3 [hp_X]/1 mL; CROCANTHEMUM CANADENSE 200 [hp_C]/1 mL; ECHINACEA ANGUSTIFOLIA WHOLE 3 [hp_X]/1 mL; GALIUM APARINE WHOLE 3 [hp_X]/1 mL; PORK LIVER 6 [hp_X]/1 mL; CALCIUM SULFIDE 30 [hp_X]/1 mL; SOMATROPIN 30 [hp_X]/1 mL; SUS SCROFA PITUITARY GLAND 30 [hp_X]/1 mL; NITRIC ACID 30 [hp_C]/1 mL; PHYTOLACCA AMERICANA ROOT 6 [hp_X]/1 mL; SULFUR 200 [hp_C]/1 mL; THUJA OCCIDENTALIS LEAFY TWIG 200 [hp_C]/1 mL; SUS SCROFA THYMUS 6 [hp_X]/1 mL
INACTIVE INGREDIENTS: WATER; ALCOHOL

DRUG FACTS:

ACTIVE INGREDIENTS:

(in each spray): 6.67% of Apis Mellifica 200C, Borax 30C, Carduus Marianus 3X, Cistus Canadensis 200C, Echinacea 3X, Galium Aparine 3X, Hepar Suis 6X, Hepar Sulphuris Calcareum 30X, Human Growth Hormone 30X, Hypophysis Suis 30X, Nitricum Acidum 30C, Phytolacca Decandra 6X, Sulphur 200C, Thuja Occidentalis 200C, Thymus Suis 6X.

PURPOSE:

May help support the body's natural defense mechanisms and may temporarily relieve symptoms such as:

• tendency towards colds or flu

• intermittent joint pain

• weakness and fatigue

• occasional sleeplessness**

**Claims based on traditional homeopathic practice, not accepted medical evidence. Not FDA evaluated.

WARNINGS:

Do not use if you have ever had an allergic reaction to this product or any of its ingredients.

Ask a doctor before use if you have been diagnosed with a condition known to weaken immunity such as HIV, the virus that causes AIDS.

Stop use and ask a doctor if symptoms persist for more than 7 days, worsen, or if new symptoms occur.

Keep out of reach of children. In case of overdose, get medical help or call a Poison Control Center right away.

If pregnant or breast-feeding, ask a health professional before use.

Do not use if TAMPER EVIDENT seal around neck of bottle is missing or broken.

Store at room temperature.

KEEP OUT OF REACH OF CHILDREN:

In case of overdose, get medical help or call a Poison Control Center right away.

DIRECTIONS:

Adults Only: Spray twice under the tongue three times a day.

This bottle contains about a 1 month supply. Some notice improvement within 2 to 3 weeks, others longer.

INDICATIONS:

May help support the body's natural defense mechanisms and may temporarily relieve symptoms such as:

• tendency towards colds or flu

• intermittent joint pain

• weakness and fatigue

• occasional sleeplessness**

**Claims based on traditional homeopathic practice, not accepted medical evidence. Not FDA evaluated.

INACTIVE INGREDIENTS:

Organic alcohol 20% v/v, Purified water.

QUESTIONS:

DIST. BY LIDDELL LABORATORIES INC.

201 APPLE BLVD.

WOODBINE, IA 51579

WWW.LIDDELL.NET

1-800-460-7733

PACKAGE LABEL DISPLAY:

VITÀL

IMMUNE

BOOSTER

with echinacea

HOMEOPATHIC

1.0 FL OZ. (30 ml)

LIDDELL®